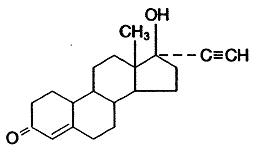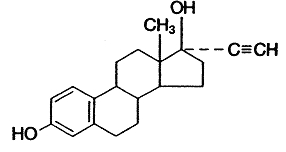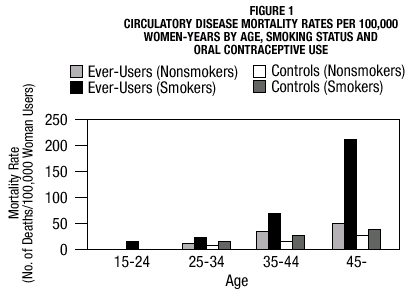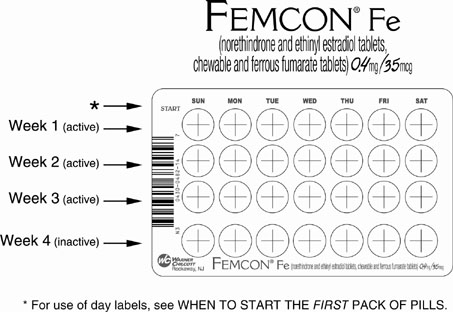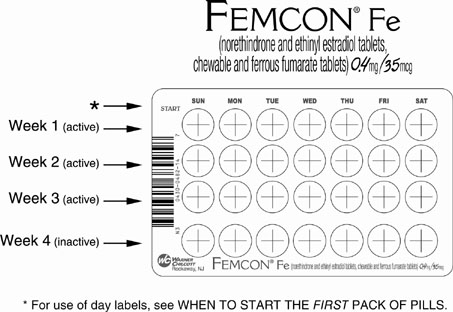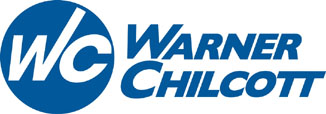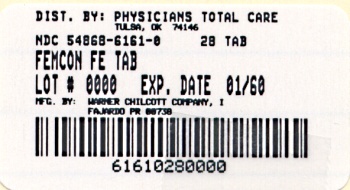 DRUG LABEL: FEMCON Fe
NDC: 54868-6161 | Form: KIT | Route: ORAL
Manufacturer: Physicians Total Care, Inc.
Category: prescription | Type: HUMAN PRESCRIPTION DRUG LABEL
Date: 20090401

ACTIVE INGREDIENTS: NORETHINDRONE ACETATE 0.4 mg/1 1; ETHINYL ESTRADIOL 0.035 mg/1 1
INACTIVE INGREDIENTS: ANHYDROUS DIBASIC CALCIUM PHOSPHATE; LACTOSE; MAGNESIUM STEARATE; MALTODEXTRIN; POVIDONE; SODIUM STARCH GLYCOLATE TYPE A POTATO; SPEARMINT; SUCRALOSE; FERROUS FUMARATE 75 mg/1 1; CELLULOSE, MICROCRYSTALLINE; MAGNESIUM STEARATE; POVIDONE; SODIUM STARCH GLYCOLATE TYPE A POTATO

FEMCON® Fe
(norethindrone and ethinyl estradiol tablets,
chewable and ferrous fumarate tablets) 0.4 mg / 35 mcg

Ferrous fumarate tablets are not USP for dissolution and assay.

Patients should be counseled that this product does not protect against HIV infection (AIDS) and other sexually transmitted diseases.

DESCRIPTION

FEMCON® Fe provides a regimen for oral contraception derived from 21 white tablets composed of norethindrone and ethinyl estradiol followed by 7 brown ferrous fumarate (placebo) tablets. The chemical name for norethindrone is 17-hydroxy-19-nor-17α-pregn-4-en-20-yn-3-one and for ethinyl estradiol the chemical name is 19-nor-17α-pregna-1,3,5(10)-trien-20-yne-3,17-diol. The structural formulas are:

NORETHINDRONE

ETHINYL ESTRADIOL

The active white FEMCON Fe tablets contain 0.4 mg norethindrone and 0.035 mg ethinyl estradiol, and the following inactive ingredients: dibasic calcium phosphate, lactose, magnesium stearate, maltodextrin, povidone, sodium starch glycolate, spearmint flavor and sucralose.

The brown tablets contain ferrous fumarate, microcrystalline cellulose, magnesium stereate, povidone, sodium starch glycolate, and compressible sugar. The ferrous fumarate tablets do not serve any therapeutic purpose.

CLINICAL PHARMACOLOGY

Combination oral contraceptives act by suppression of gonadotropins. Although the primary mechanism of this action is inhibition of ovulation, other alterations include changes in the cervical mucus (which increase the difficulty of sperm entry into the uterus) and the endometrium (which reduce the likelihood of implantation).

Absorption

Ethinyl estradiol and norethindrone are rapidly absorbed with maximum plasma concentrations occurring within 2 hours after FEMCON Fe administration (see Table 1). Norethindrone appears to be completely absorbed following oral administration; however, it is subject to first-pass metabolism resulting in an absolute bioavailability of approximately 65%. Large intersubject variability is reflected in a 3- to 5-fold variation in norethindrone bioavailability. Ethinyl estradiol bioavailability is approximately 43% due to small-intestinal and hepatic first-pass metabolism.

Table 1. Mean ±SD Pharmacokinetic Parameters Following Single Dose Administration of FEMCON Fe in Healthy Female Subjects Under Fasting Conditions.
Norethindrone/Ethinyl Estradiol | tmax (h) | Cmax (pg/mL) | AUC0-∞ (pg•h/mL) | t1/2 (h)
Norethindrone 0.4 mg | 1.24 ± 0.40 [n = 26] | 4210.6 ± 1628.8 | 18034.9 ± 7852.9 [n = 25] | 8.6 ± 3.7
Ethinyl Estradiol 35 mcg | 1.44 ± 0.33 | 131.4 ± 34.2 | 1065.8 ± 276.2 | 17.1 ± 4.4
Cmax = maximum plasma concentration; tmax = time to reach Cmax; AUC = area under the curve; t1/2 = elimination half life.

Effect of Food. Single-dose administration of FEMCON Fe tablets with food decreased the maximum norethindrone and ethinyl estradiol concentration by 53% and 47%, respectively; the extent of norethindrone and ethinyl estradiol absorption (AUC values) was not affected by food administration.

Distribution

Norethindrone is 36% bound to sex hormone-binding globulin (SHBG) and 61% bound to albumin. Ethinyl estradiol is not bound to SHBG but is highly (98.5%) bound to albumin. Volume of distribution of norethindrone and ethinyl estradiol ranges from 2 to 4 L/kg.

Metabolism

Norethindrone undergoes extensive biotransformation, primarily via reduction, followed by sulfate and glucuronide conjugation; less than 5% of a norethindrone dose is excreted unchanged; greater than 50% and 20-40% of a dose is excreted in urine and feces, respectively. The majority of metabolites in the circulation are sulfates, with glucuronides accounting for most of the urinary metabolites.

Ethinyl estradiol is also extensively metabolized, both by oxidation and by conjugation with sulfate and glucuronide. Sulfates are the major circulating conjugates of ethinyl estradiol, and glucuronides predominate in urine. The primary oxidative metabolite is 2-hydroxy-ethinyl estradiol which is formed by the CYP3A4 isoform of cytochrome P450.

Excretion

Plasma clearance values for norethindrone and ethinyl estradiol are similar (approximately 0.4 L/hr/kg). Ethinyl estradiol and norethindrone are excreted in both urine and feces, primarily as metabolites. Ethinyl estradiol is excreted in urine and feces as glucuronides and sulfates, and about 28-43% undergoes enterohepatic circulation. The mean terminal elimination half-lives of norethindrone and ethinyl estradiol following single dose administration of FEMCON Fe are approximately 9 hours and 17 hours, respectively.

Special Populations

Race. The effect of race on the disposition of norethindrone and ethinyl estradiol after FEMCON Fe administration has not been evaluated.

Renal Insufficiency. The effect of renal disease on the disposition of norethindrone and ethinyl estradiol after FEMCON Fe administration has not been evaluated. In premenopausal women with chronic renal failure undergoing peritoneal dialysis who received multiple doses of an oral contraceptive containing ethinyl estradiol and norethindrone, plasma ethinyl estradiol concentrations were higher and norethindrone concentrations were unchanged compared to concentrations in premenopausal women with normal renal function.

Hepatic Insufficiency. The effect of hepatic disease on the disposition of norethindrone and ethinyl estradiol after FEMCON Fe administration has not been evaluated. However, ethinyl estradiol and norethindrone may be poorly metabolized in patients with impaired liver function.

Drug-Drug Interactions

See PRECAUTIONS section—DRUG INTERACTIONS

INDICATIONS AND USAGE

FEMCON Fe is indicated for the prevention of pregnancy in women who elect to use this product as a method of contraception.

Oral contraceptives are highly effective. Table 2 lists the typical unintended pregnancy rates for users of combination oral contraceptives and other methods of contraception. The efficacy of these contraceptive methods, except sterilization, the IUD, and implants, depends upon the reliability with which they are used. Correct and consistent use of methods can result in lower failure rates.

TABLE 2 Percentage of women experiencing an unintended pregnancy during the first year of typical use and the first year of perfect use of contraception and the percentage continuing use at the end of the first year. United States.
 | % of Women Experiencing an Unintended; Pregnancy within the First Year of Use |  | % of Women; Continuing Use at One Year
Method; (1) | Typical Use; (2) | Perfect Use; (3) | (4)
Chance | 85 | 85
Spermicides | 26 | 6 | 40
Periodic abstinence | 25 |  | 63
Calendar |  | 9
Ovulation Method |  | 3
Sympto-thermal |  | 2
Post-Ovulation |  | 1
Cap [With spermicidal cream or jelly]
Parous Women | 40 | 26 | 42
Nulliparous Women | 20 | 9 | 56
Sponge
Parous Women | 40 | 20 | 42
Nulliparous Women | 20 | 9 | 56
Diaphragm | 20 | 6 | 56
Withdrawal | 19 | 4
Condom
Female (reality) | 21 | 5 | 56
Male | 14 | 3 | 61
Pill | 5 |  | 71
Progestin only |  | 0.5
Combined |  | 0.1
IUD
Progesterone T | 2.0 | 1.5 | 81
Copper T 380A | 0.8 | 0.6 | 78
LNg 20 | 0.1 | 0.1 | 81
Depo-Provera® | 0.3 | 0.3 | 70
Norplant® and Norplant® 2 | 0.05 | 0.05 | 88
Female Sterilization | 0.5 | 0.5 | 100
Male Sterilization | 0.15 | 0.10 | 100
Emergency Contraceptive Pills: Treatment initiated within 72 hours after unprotected intercourse reduces risk of pregnancy by at least 75%
Lactational Amenorrhea Method: LAM is a highly effective, temporary method of contraception
Source: Trussell J, Stewart F, Contraceptive Efficacy. In Hatcher RA, Trussell J, Stewart F, Cates W, Stewart GK, Kowal D, Guest F, Contraceptive Technology: Seventeenth Revised Edition. New York, NY: Irvington Publishers, 1998.

CONTRAINDICATIONS

Combination oral contraceptives should not be used in women who currently have the following conditions:

- Thrombophlebitis or thromboembolic disorders
- History of deep vein thrombophlebitis or thromboembolic disorders
- Cerebrovascular or coronary artery disease (current or history)
- Valvular heart disease with thrombogenic complications
- Uncontrolled hypertension
- Diabetes with vascular involvement
- Headaches with focal neurological symptoms, such as aura
- Major surgery with prolonged immobilization
- Known or suspected carcinoma of the breast or personal history of breast cancer
- Carcinoma of the endometrium or other known or suspected estrogen-dependent neoplasia
- Undiagnosed abnormal genital bleeding
- Cholestatic jaundice of pregnancy or jaundice with prior pill use
- Hepatic adenomas or carcinomas, or active liver disease
- Known or suspected pregnancy
- Hypersensitivity to any component of this product

WARNINGS

BOXED WARNING

Cigarette smoking increases the risk of serious cardiovascular side effects from oral contraceptive use. This risk increases with age and with the extent of smoking (in epidemiologic studies, 15 or more cigarettes per day was associated with a significantly increased risk) and is quite marked in women over 35 years of age. Women who use oral contraceptives should be strongly advised not to smoke.

The use of oral contraceptives is associated with increased risk of several serious conditions including venous and arterial thrombotic and thromboembolic events (such as myocardial infarction, thromboembolism, and stroke), hepatic neoplasia, gallbladder disease, and hypertension, although the risk of serious morbidity or mortality is very small in healthy women without underlying risk factors. The risk of morbidity and mortality increases significantly in the presence of other underlying risk factors such as certain inherited thrombophilias, hypertension, hyperlipidemias, obesity and diabetes.

Practitioners prescribing oral contraceptives should be familiar with the following information relating to these risks. The information contained in this package insert is principally based on studies carried out in patients who used oral contraceptives with higher formulations of estrogens and progestogens than those in common use today. The effect of long-term use of the oral contraceptives with lower formulations of both estrogens and progestogens remains to be determined.

Throughout this labeling, epidemiological studies reported are of two types: retrospective or case control studies and prospective or cohort studies. Case control studies provide a measure of the relative risk of a disease, namely, a ratio of the incidence of a disease among oral contraceptive users to that among nonusers. The relative risk does not provide information on the actual clinical occurrence of a disease. Cohort studies provide a measure of attributable risk, which is the difference in the incidence of disease between oral contraceptive users and nonusers. The attributable risk does provide information about the actual occurrence of a disease in the population. For further information, the reader is referred to a text on epidemiological methods.

1. THROMBOEMBOLIC DISORDERS AND OTHER VASCULAR PROBLEMS

a. Myocardial Infarction

An increased risk of myocardial infarction has been attributed to oral contraceptive use. This risk is primarily in smokers or women with other underlying risk factors for coronary artery disease such as hypertension, hypercholesterolemia, morbid obesity, and diabetes. The relative risk of heart attack for current oral contraceptive users has been estimated to be two to six. The risk is very low under the age of 30.

Smoking in combination with oral contraceptive use has been shown to contribute substantially to the incidence of myocardial infarctions in women in their mid-thirties or older, with smoking accounting for the majority of excess cases. Mortality rates associated with circulatory disease have been shown to increase substantially in smokers over the age of 35 and nonsmokers over the age of 40 (Figure 1) among women who use oral contraceptives.

Layde PM, Beral V. Lancet 1981;1:541-546.

Oral contraceptives may compound the effects of well-known risk factors, such as hypertension, diabetes, hyperlipidemias, age, and obesity. In particular, some progestogens are known to decrease HDL cholesterol and cause glucose intolerance, while estrogens may create a state of hyperinsulinism. Oral contraceptives have been shown to increase blood pressure among users (see section 9 in WARNINGS). Such increases in risk factors have been associated with an increased risk of heart disease and the risk increases with the number of risk factors present. Oral contraceptives must be used with caution in women with cardiovascular disease risk factors.

b. Thromboembolism

An increased risk of thromboembolic and thrombotic disease associated with the use of oral contraceptives is well established. Case control studies have found the relative risk of users compared to non-users to be 3 for the first episode of superficial venous thrombosis, 4 to 11 for deep vein thrombosis or pulmonary embolism, and 1.5 to 6 for women with predisposing conditions for venous thromboembolic disease. Cohort studies have shown the relative risk to be somewhat lower, about 3 for new cases and about 4.5 for new cases requiring hospitalization. The approximate incidence of deep-vein thrombosis and pulmonary embolism in users of low dose (<50 mcg ethinyl estradiol) combination oral contraceptives is up to 4 per 10,000 woman-years compared to 0.5-3 per 10,000 woman-years for non-users. However, the incidence is substantially less than that associated with pregnancy (6 per 10,000 woman-years). The risk of thromboembolic disease due to oral contraceptives is not related to length of use and disappears after pill use is stopped.

A two- to four-fold increase in relative risk of postoperative thromboembolic complications has been reported with the use of oral contraceptives. The relative risk of venous thrombosis in women who have predisposing conditions is twice that of women without such medical conditions. If feasible, oral contraceptives should be discontinued at least four weeks prior to and for two weeks after elective surgery of a type associated with an increase in risk of thromboembolism and during and following prolonged immobilization. Since the immediate postpartum period is also associated with an increased risk of thromboembolism, oral contraceptives should be started no earlier than four to six weeks after delivery in women who elect not to breastfeed.

c. Cerebrovascular diseases

Oral contraceptives have been shown to increase both the relative and attributable risk of cerebrovascular events (thrombotic and hemorrhagic strokes) although, in general, the risk is greatest among older (>35 years), hypertensive women who also smoke. Hypertension was found to be a risk factor for both users and nonusers, for both types of strokes, while smoking interacted to increase the risk for hemorrhagic strokes.

In a large study, the relative risk of thrombotic strokes has been shown to range from 3 for normotensive users to 14 for users with severe hypertension. The relative risk of hemorrhagic stroke is reported to be 1.2 for nonsmokers who used oral contraceptives, 2.6 for smokers who did not use oral contraceptives, 7.6 for smokers who used oral contraceptives, 1.8 for normotensive users and 25.7 for users with severe hypertension. The attributable risk is also greater in older women. Oral contraceptives also increase the risk for stroke in women with other underlying risk factors such as certain inherited or acquired thrombophilias, hyperlipidemias, and obesity. Women with migraine (particularly migraine with aura) who take combination oral contraceptives may be at an increased risk of stroke.

d. Dose-related risk of vascular disease from oral contraceptives

A positive association has been observed between the amount of estrogen and progestogen in oral contraceptives and the risk of vascular disease. A decline in serum high density lipoproteins (HDL) has been reported with many progestational agents. A decline in serum high density lipoproteins has been associated with an increased incidence of ischemic heart disease. Because estrogens increase HDL cholesterol, the net effect of an oral contraceptive depends on a balance achieved between doses of estrogen and progestogen and the nature and absolute amount of progestogens used in the contraceptive. The amount of both hormones should be considered in the choice of an oral contraceptive.

Minimizing exposure to estrogen and progestogen is in keeping with good principles of therapeutics. For any particular estrogen/progestogen combination, the dosage regimen prescribed should be one which contains the least amount of estrogen and progestogen that is compatible with a low failure rate and the needs of the individual patient. New acceptors of oral contraceptive agents should be started on preparations containing the lowest estrogen content which is judged appropriate for the individual patient.

e. Persistence of risk of vascular disease

There are two studies which have shown persistence of risk of vascular disease for ever-users of oral contraceptives. In a study in the United States, the risk of developing myocardial infarction after discontinuing oral contraceptives persists for at least 9 years for women 40-49 years old who had used oral contraceptives for five or more years but this increased risk was not demonstrated in other age groups.

In another study in Great Britain, the risk of developing cerebrovascular disease persisted for at least 6 years after discontinuation of oral contraceptives, although excess risk was very small. However, both studies were performed with oral contraceptive formulations containing 50 micrograms or higher of estrogens.

2. ESTIMATES OF MORTALITY FROM CONTRACEPTIVE USE

One study gathered data from a variety of sources which have estimated the mortality rate associated with different methods of contraception at different ages (Table 3).

TABLE 3 ANNUAL NUMBER OF BIRTH-RELATED OR METHOD-RELATED DEATHS ASSOCIATED WITH CONTROL OF FERTILITY PER 100,000 NONSTERILE WOMEN, BY FERTILITY CONTROL METHOD ACCORDING TO AGE
 | AGE
Method of control; and outcome | 15-19 | 20-24 | 25-29 | 30-34 | 35-39 | 40-44
No fertility control methods* | 7.0 | 7.4 | 9.1 | 14.8 | 25.7 | 28.2
Oral contraceptives; nonsmoker** | 0.3 | 0.5 | 0.9 | 1.9 | 13.8 | 31.6
Oral contraceptives; smoker** | 2.2 | 3.4 | 6.6 | 13.5 | 51.1 | 117.2
IUD** | 0.8 | 0.8 | 1.0 | 1.0 | 1.4 | 1.4
Condom* | 1.1 | 1.6 | 0.7 | 0.2 | 0.3 | 0.4
Diaphragm/spermicide* | 1.9 | 1.2 | 1.2 | 1.3 | 2.2 | 2.8
Periodic abstinence* | 2.5 | 1.6 | 1.6 | 1.7 | 2.9 | 3.6
*Deaths are birth related
**Deaths are method related
Ory HW. Family Planning Perspectives 1983; 15:57-63.

These estimates include the combined risk of death associated with contraceptive methods plus the risk attributable to pregnancy in the event of method failure. Each method of contraception has its specific benefits and risk. The study concluded that with the exception of oral contraceptive users 35 and older who smoke and 40 and older who do not smoke, mortality associated with all methods of birth control is low and below that associated with childbirth.

The observation of a possible increase in risk of mortality with age for oral contraceptive users is based on data gathered in the 1970s but not reported until 1983. However, current clinical practice involves the use of lower estrogen dose formulations combined with careful restriction of oral contraceptive use to women who do not have the various risk factors listed in this labeling.

Because of these changes in practice and, also, because of some limited new data which suggest that the risk of cardiovascular disease with the use of oral contraceptives may now be less than previously observed, the Fertility and Maternal Health Drugs Advisory Committee was asked to review the topic in 1989. The Committee concluded that although cardiovascular disease risk may be increased with oral contraceptive use after age 40 in healthy nonsmoking women (even with the newer low-dose formulations), there are greater potential health risks associated with pregnancy in older women and with the alternative surgical and medical procedures which may be necessary if such women do not have access to effective and acceptable means of contraception.

Therefore, the Committee recommended that the benefits of oral contraceptive use by healthy nonsmoking women over 40 may outweigh the possible risks. Of course, older women, as all women who take oral contraceptives, should take the lowest possible dose formulation that is effective.

3. CARCINOMA OF THE REPRODUCTIVE ORGANS AND BREASTS

Numerous epidemiological studies have been performed on the incidence of breast, endometrial, ovarian, and cervical cancer in women using oral contraceptives. Although the risk of breast cancer may be slightly increased among current users of oral contraceptives (RR = 1.24), this excess risk decreases over time after oral contraceptive discontinuation and by 10 years after cessation the increased risk disappears. The risk does not increase with duration of use, and no relationships have been found with dose or type of steroid. The patterns of risk are also similar regardless of a woman's reproductive history or her family breast cancer history. The subgroup for whom risk has been found to be significantly elevated is women who first used oral contraceptives before age 20, but because breast cancer is so rare at these young ages, the number of cases attributable to this early oral contraceptive use is extremely small. Breast cancers diagnosed in current or previous oral contraceptive users tend to be less advanced clinically than in never-users. Women who currently have or have had breast cancer should not use oral contraceptives because breast cancer is a hormone-sensitive tumor.

Some studies suggest that oral contraceptive use has been associated with an increase in the risk of cervical intraepithelial neoplasia or invasive cervical cancer in some populations of women. However, there continues to be controversy about the extent to which such findings may be due to differences in sexual behavior and other factors.

In spite of many studies of the relationship between oral contraceptive use and breast cancer and cervical cancers, a cause-and-effect relationship has not been established.

4. HEPATIC NEOPLASIA

Benign hepatic adenomas are associated with oral contraceptive use, although their occurrence is rare in the United States. Indirect calculations have estimated the attributable risk to be in the range of 3.3 cases/100,000 for users, a risk that increases after four or more years of use. Rupture of hepatic adenomas may cause death through intra-abdominal hemorrhage.

Studies from Britain have shown an increased risk of developing hepatocellular carcinoma in long-term (>8 years) oral contraceptive users. However, these cancers are extremely rare in the U.S. and the attributable risk (the excess incidence) of liver cancers in oral contraceptive users approaches less than one per million users.

5. OCULAR LESIONS

There have been clinical case reports of retinal thrombosis associated with the use of oral contraceptives that may lead to partial or complete loss of vision. Oral contraceptives should be discontinued if there is unexplained partial or complete loss of vision; onset of proptosis or diplopia; papilledema; or retinal vascular lesions. Appropriate diagnostic and therapeutic measures should be undertaken immediately.

6. ORAL CONTRACEPTIVE USE BEFORE OR DURING EARLY PREGNANCY

Extensive epidemiological studies have revealed no increased risk of birth defects in women who have used oral contraceptives prior to pregnancy. Studies also do not suggest a teratogenic effect, particularly in so far as cardiac anomalies and limb reduction defects are concerned, when taken inadvertently during early pregnancy (see CONTRAINDICATIONS section).

The administration of oral contraceptives to induce withdrawal bleeding should not be used as a test for pregnancy. Oral contraceptives should not be used during pregnancy to treat threatened or habitual abortion.

It is recommended that for any patient who has missed two consecutive periods, pregnancy should be ruled out. If the patient has not adhered to the prescribed schedule, the possibility of pregnancy should be considered at the time of the first missed period. Oral contraceptive use should be discontinued if pregnancy is confirmed.

7. GALLBLADDER DISEASE

Earlier studies have reported an increased lifetime relative risk of gallbladder surgery in users of oral contraceptives and estrogens. More recent studies, however, have shown that the relative risk of developing gallbladder disease among oral contraceptive users may be minimal. The recent findings of minimal risk may be related to the use of oral contraceptive formulations containing lower hormonal doses of estrogens and progestogens.

8. CARBOHYDRATE AND LIPID METABOLIC EFFECTS

Oral contraceptives have been shown to cause glucose intolerance in a significant percentage of users. Oral contraceptives containing greater than 75 micrograms of estrogens cause hyperinsulinism, while lower doses of estrogen cause less glucose intolerance. Progestogens increase insulin secretion and create insulin resistance, this effect varying with different progestational agents. However, in the nondiabetic woman, oral contraceptives appear to have no effect on fasting blood glucose. Because of these demonstrated effects, prediabetic and diabetic women should be carefully observed while taking oral contraceptives.

A small proportion of women will have persistent hypertriglyceridemia while on the pill. As discussed earlier (see WARNINGS 1.a. and 1.d.), changes in serum triglycerides and lipoprotein levels have been reported in oral contraceptive users.

9. ELEVATED BLOOD PRESSURE

Women with significant hypertension should not be started on hormonal contraceptives. An increase in blood pressure has been reported in women taking oral contraceptives, and this increase is more likely in older oral contraceptive users and with continued use. Data from the Royal College of General Practitioners and subsequent randomized trials have shown that the incidence of hypertension increases with increasing concentrations of progestogens.

Women with a history of hypertension or hypertension-related diseases, or renal disease should be encouraged to use another method of contraception. If women elect to use oral contraceptives, they should be monitored closely and if significant elevation of blood pressure occurs, oral contraceptives should be discontinued (see CONTRAINDICATIONS section). For most women, elevated blood pressure will return to normal after stopping oral contraceptives, and there is no difference in the occurrence of hypertension among ever- and never-users.

10. HEADACHE

The onset or exacerbation of migraine or development of headache with a new pattern which is recurrent, persistent, or severe requires discontinuation of oral contraceptives and evaluation of the cause (see WARNINGS 1.c.).

11. BLEEDING IRREGULARITIES

Breakthrough bleeding and spotting are sometimes encountered in patients on oral contraceptives, especially during the first three months of use. If bleeding persists or recurs, nonhormonal causes should be considered and adequate diagnostic measures taken to rule out malignancy or pregnancy as in the case of any abnormal vaginal bleeding. If pathology has been excluded, time or a change to another formulation may solve the problem. In the event of amenorrhea, pregnancy should be ruled out.

Some women may encounter post-pill amenorrhea or oligomenorrhea (possibly with anovulation), especially when such a condition was preexistent.

12. ECTOPIC PREGNANCY

Ectopic as well as intrauterine pregnancy may occur in contraceptive failures.

PRECAUTIONS

1. SEXUALLY TRANSMITTED DISEASES

Patients should be counseled that this product does not protect against HIV infection (AIDS) and other sexually transmitted diseases.

2. PHYSICAL EXAMINATION AND FOLLOW-UP

A periodic personal and family medical history and complete physical examination are appropriate for all women, including women using oral contraceptives. The physical examination, however, may be deferred until after initiation of oral contraceptives if requested by the woman and judged appropriate by the clinician. The physical examination should include special reference to blood pressure, breasts, abdomen and pelvic organs, including cervical cytology, and relevant laboratory tests. In case of undiagnosed, persistent or recurrent abnormal vaginal bleeding, appropriate measures should be conducted to rule out malignancy. Women with a strong family history of breast cancer or who have breast nodules should be monitored with particular care.

3. LIPID DISORDERS

Women who are being treated for hyperlipidemias should be followed closely if they elect to use oral contraceptives. Some progestogens may elevate LDL levels and may render the control of hyperlipidemias more difficult. (See WARNINGS 1.d.)

In patients with familial defects of lipoprotein metabolism receiving estrogen-containing preparations, there have been case reports of significant elevations of plasma triglycerides leading to pancreatitis.

4. LIVER FUNCTION

If jaundice develops in any woman receiving such drugs, the medication should be discontinued. Steroid hormones may be poorly metabolized in patients with impaired liver function.

5. FLUID RETENTION

Oral contraceptives may cause some degree of fluid retention. They should be prescribed with caution, and only with careful monitoring, in patients with conditions which might be aggravated by fluid retention.

6. EMOTIONAL DISORDERS

Women with a history of depression should be carefully observed and the drug discontinued if depression recurs to a serious degree. Patients becoming significantly depressed while taking oral contraceptives should stop the medication and use an alternate method of contraception in an attempt to determine whether the symptom is drug related. Women with a history of depression should be carefully observed and the drug discontinued if depression recurs to a serious degree.

7. CONTACT LENSES

Contact lens wearers who develop visual changes or changes in lens tolerance should be assessed by an ophthalmologist.

8. DRUG INTERACTIONS

Changes in contraceptive effectiveness associated with co-administration of other products:

a. Anti-infective agents and anticonvulsants

Contraceptive effectiveness may be reduced when hormonal contraceptives are co-administered with antibiotics, anticonvulsants, and other drugs that increase the metabolism of contraceptive steroids. This could result in unintended pregnancy or breakthrough bleeding. Examples include rifampin, barbiturates, phenylbutazone, phenytoin, carbamazepine, felbamate, oxcarbazepine, topiramate, and griseofulvin. Several cases of contraceptive failure and breakthrough bleeding have been reported in the literature with concomitant administration of antibiotics such as ampicillin and tetracyclines. However, clinical pharmacology studies investigating drug interaction between combined oral contraceptives and these antibiotics have reported inconsistent results.

b. Anti-HIV protease inhibitors

Several of the anti-HIV protease inhibitors have been studied with co-administration of oral combination hormonal contraceptives; significant changes (increase and decrease) in the plasma levels of the estrogen and progestin have been noted in some cases. The safety and efficacy of combination oral contraceptive products may be affected with co-administration of anti-HIV protease inhibitors. Healthcare providers should refer to the label of the individual anti-HIV protease inhibitors for further drug-drug interaction information.

c. Herbal products

Herbal products containing St. John’s Wort (hypericum perforatum) may induce hepatic enzymes (cytochrome P450) and p-glycoprotein transporter and may reduce the effectiveness of contraceptive steroids. This may also result in breakthrough bleeding.

Increase in plasma levels of estradiol associated with co-administered drugs:

Co-administration of atorvastatin and certain combination oral contraceptives containing ethinyl estradiol increase AUC values for ethinyl estradiol by approximately 20%. Ascorbic acid and acetaminophen may increase plasma ethinyl estradiol levels, possibly by inhibition of conjugation. CYP3A4 inhibitors such as itraconazole or ketoconazole may increase plasma hormone levels.

Changes in plasma levels of co-administered drugs:

Combination hormonal contraceptives containing some synthetic estrogens (e.g., ethinyl estradiol) may inhibit the metabolism of other compounds. Increased plasma concentrations of cyclosporin, prednisolone, and theophylline have been reported with concomitant administration of combination oral contraceptives. Decreased plasma concentrations of acetaminophen and increased clearance of temazepam, salicylic acid, morphine and clofibric acid, due to induction of conjugation have been noted when these drugs were administered with combination oral contraceptives.

9. INTERACTIONS WITH LABORATORY TESTS

Certain endocrine and liver function tests and blood components may be affected by oral contraceptives:

1. Increased prothrombin and factors VII, VIII, IX, and X; decreased antithrombin 3; increased norepinephrine-induced platelet aggregability.
2. Increased thyroid-binding globulin (TBG) leading to increased circulating total thyroid hormone, as measured by protein-bound iodine (PBI), T4 by column or by radioimmunoassay. Free T3 resin uptake is decreased, reflecting the elevated TBG, free T4 concentration is unaltered.
3. Other binding proteins may be elevated in serum.
4. Sex hormone binding globulins are increased and result in elevated levels of total circulating sex steroids and corticoids; however, free or biologically active levels remain unchanged.
5. Triglycerides may be increased and levels of various other lipids and lipoproteins may be affected.
6. Glucose tolerance may be decreased.
7. Serum folate levels may be depressed by oral contraceptive therapy. This may be of clinical significance if a woman becomes pregnant shortly after discontinuing oral contraceptives.

10. CARCINOGENESIS

See WARNINGS section.

11. PREGNANCY

Pregnancy Category X. See CONTRAINDICATIONS and WARNINGS sections.

12. NURSING MOTHERS

Small amounts of oral contraceptive steroids and/or metabolites have been identifed in the milk of nursing mothers and a few adverse effects on the child have been reported, including jaundice and breast enlargement. In addition, combination oral contraceptives given in the postpartum period may interfere with lactation by decreasing the quantity and quality of breast milk. If possible, the nursing mother should be advised not to use combination oral contraceptives but to use other forms of contraception until she has completely weaned her child.

13. PEDIATRIC USE

Safety and efficacy of FEMCON Fe have been established in women of reproductive age. Safety and efficacy are expected to be the same in postpubertal adolescents under the age of 16 years and in users ages 16 years and older. Use of this product before menarche is not indicated.

14. GERIATRIC USE

This product has not been studied in women over 65 years of age and is not indicated in this population.

INFORMATION FOR THE PATIENT

See Patient Labeling printed below

ADVERSE REACTIONS

An increased risk of the following serious adverse reactions has been associated with the use of oral contraceptives (see WARNINGS section):

- Thrombophlebitis
- Arterial thromboembolism
- Pulmonary embolism
- Myocardial infarction
- Cerebral hemorrhage
- Cerebral thrombosis
- Hypertension
- Gallbladder disease
- Hepatic adenomas or benign liver tumors

There is evidence of an association between the following conditions and the use of oral contraceptives:

- Mesenteric thrombosis
- Retinal thrombosis

The following adverse reactions have been reported in patients receiving oral contraceptives and are believed to be drug related:

- Nausea
- Vomiting
- Gastrointestinal symptoms (such as abdominal pain, cramps and bloating)
- Breakthrough bleeding
- Spotting
- Change in menstrual flow
- Amenorrhea
- Temporary infertility after discontinuation of treatment
- Edema/fluid retention
- Melasma/chloasma which may persist
- Breast changes: tenderness, pain, enlargement, and secretion
- Change in weight or appetite (increase or decrease)
- Change in cervical ectropion and secretion
- Possible diminution in lactation when given immediately postpartum
- Cholestatic jaundice
- Migraine headache
- Rash (allergic)
- Mood changes, including depression
- Vaginitis, including candidiasis
- Change in corneal curvature (steepening)
- Intolerance to contact lenses
- Decrease in serum folate levels
- Exacerbation of systemic lupus erythematosus
- Exacerbation of porphyria
- Exacerbation of chorea
- Aggravation of varicose veins
- Anaphylactic/anaphylactoid reactions, including urticaria, angioedema, and severe reactions with respiratory and circulatory symptoms

The following adverse reactions have been reported in users of oral contraceptives, and a causal association has been neither confirmed nor refuted:

- Premenstrual syndrome
- Cataracts
- Optic neuritis, which may lead to partial or complete loss of vision
- Cystitis-like syndrome
- Headache
- Nervousness
- Dizziness
- Hirsutism
- Loss of scalp hair
- Erythema multiforme
- Erythema nodosum
- Hemorrhagic eruption
- Impaired renal function
- Hemolytic uremic syndrome
- Budd-Chiari syndrome
- Acne
- Changes in libido
- Colitis
- Pancreatitis
- Dysmenorrhea

OVERDOSAGE

Serious ill effects have not been reported following acute ingestion of large doses of oral contraceptives by young children. Overdosage may cause nausea, and withdrawal bleeding may occur in females.

NONCONTRACEPTIVE HEALTH BENEFITS

The following noncontraceptive health benefits related to the use of oral contraceptives are supported by epidemiological studies which largely utilized oral contraceptive formulations containing doses exceeding 0.035 mg of ethinyl estradiol or 0.05 mg of mestranol.

Effects on menses:

- Increased menstrual cycle regularity
- Decreased blood loss and decreased incidence of iron-deficiency anemia
- Decreased incidence of dysmenorrhea

Effects related to inhibition of ovulation:

- Decreased incidence of functional ovarian cysts
- Decreased incidence of ectopic pregnancies

Effects from long-term use:

- Decreased incidence of fibroadenomas and fibrocystic disease of the breast
- Decreased incidence of acute pelvic inflammatory disease
- Decreased incidence of endometrial cancer
- Decreased incidence of ovarian cancer

DOSAGE AND ADMINISTRATION

To achieve maximum contraceptive effectiveness, FEMCON Fe must be taken exactly as directed and at intervals not exceeding 24 hours. The dosage of FEMCON Fe is one white tablet daily for 21 consecutive days, followed by one brown tablet daily for 7 consecutive days. It is recommended that tablets be taken at the same time each day. The pill may be swallowed whole or chewed and swallowed. If the pill is chewed, the patient should drink a full glass (8 ounces) of liquid immediately after swallowing. During the first cycle of use, the patient is instructed to begin taking FEMCON Fe on either Day 1 or the first Sunday after the onset of menstruation. If menstruation begins on a Sunday, the first tablet (white) is taken that day. One white tablet should be taken daily for 21 consecutive days followed by one brown tablet daily for 7 consecutive days. Withdrawal bleeding should usually occur within three days following discontinuation of white tablets and may not have finished before the next pack is started. During the first cycle with a Sunday start, contraceptive reliance should not be placed on FEMCON Fe until a white tablet has been taken daily for 7 consecutive days and a non-hormonal back-up method of birth control (such as condoms or spermicide) should be used during those 7 days. The possibility of ovulation and conception prior to initiation of medication should be considered.

The patient begins her next and all subsequent 28-day courses of tablets on the same day of the week on which she began her first course, following the same schedule: 21 days on white tablets—7 days on brown tablets. If in any cycle the patient starts tablets later than the proper day, she should protect herself against pregnancy by using a non-hormonal back-up method of birth control until she has taken a white tablet daily for 7 consecutive days.

When the patient is switching from a 21-day regimen of tablets, she should wait 7 days after her last tablet before she starts FEMCON Fe. She will probably experience withdrawal bleeding during that week. She should be sure that no more than 7 days pass after her previous 21-day regimen. When the patient is switching from a 28-day regimen of tablets, she should start her first pack of FEMCON Fe on the day after her last tablet. She should not wait any days between packs. The patient may switch any day from a progestin-only pill and should begin FEMCON Fe the next day. If switching from an implant or injection, the patient should start FEMCON Fe on the day of implant removal or, if using an injection, the day the next injection would be due.

If spotting or breakthrough bleeding occurs, the patient is instructed to continue on the same regimen. This type of bleeding is usually transient and without significance; however, if the bleeding is persistent or prolonged, the patient is advised to consult her healthcare provider. Although pregnancy is unlikely if FEMCON Fe is taken according to directions, if withdrawal bleeding does not occur, the possibility of pregnancy must be considered. If the patient has not adhered to the prescribed schedule (missed one or more tablets or started taking them on a day later than she should have), the probability of pregnancy should be considered at the time of the first missed period and appropriate diagnostic measures taken. If the patient has adhered to the prescribed regimen and misses two consecutive periods, pregnancy should be ruled out. Hormonal contraceptives should be discontinued if pregnancy is confirmed.

For additional patient instructions regarding missed pills, see the “WHAT TO DO IF YOU MISS PILLS” section in the DETAILED PATIENT LABELING. Any time the patient misses two or more white tablets, she should also use another method of non-hormonal back-up contraception until she has taken a white tablet daily for seven consecutive days. If the patient misses one or more brown tablets, she is still protected against pregnancy provided she begins taking white tablets again on the proper day. If breakthrough bleeding occurs following missed white tablets, it will usually be transient and of no consequence. The possibility of ovulation increases with each successive day that scheduled white tablets are missed. The risk of pregnancy increases with each active (white) tablet missed.

FEMCON Fe may be initiated no earlier than day 28 postpartum in the nonlactating mother due to the increased risk for thromboembolism. When the tablets are administered in the postpartum period, the increased risk of thromboembolic disease associated with the postpartum period must be considered (see CONTRAINDICATIONS, WARNINGS, and PRECAUTIONS concerning thromboembolic disease). The patient should be advised to use a non-hormonal back-up method for the first 7 days of tablet-taking. However, if intercourse has already occurred, the possibility of ovulation and conception prior to initiation of medication should be considered. FEMCON Fe may be initiated after a first-trimester abortion; if the patient starts FEMCON Fe immediately, additional contraceptive measures are not needed.

For additional patient instructions regarding complete dosing instructions, see the “HOW TO TAKE THE PILL” section in the DETAILED PATIENT LABELING.

HOW SUPPLIED

FEMCON® Fe (norethindrone and ethinyl estradiol tablets, chewable and ferrous fumarate tablets) is available only in a 28-day regimen. Each package contains 21 round, white tablets of 0.4 mg norethindrone and 0.035 mg ethinyl estradiol, imprinted with W|C on one side and 581 on the other. Each brown, round tablet contains 75 mg ferrous fumarate, imprinted with PD 622 on one side.

FEMCON® Fe

NDC 54868-6161-0 Blister Card of 28 Tablets Each

STORAGE AND HANDLING

Store at 25° C (77° F); excursions permitted to 15° - 30° C (59° - 86° F) [see USP Controlled Room Temperature].

References are available upon request.

PATIENT BRIEF SUMMARY

This product (like all oral contraceptives) is intended to prevent pregnancy. It does not protect against HIV infection (AIDS) and other sexually transmitted diseases.

Oral contraceptives, also known as "birth control pills" or "the pill", are taken to prevent pregnancy, and when taken correctly without missing any pills, have a failure rate of about 1% per year (1 pregnancy per 100 women per year of use). The typical failure rate of pill users is 5% per year (5 pregnancies per 100 women per year of use) when women who miss pills are included.

For the majority of women, oral contraceptives can be taken safely. But for some women oral contraceptive use is associated with certain serious diseases that can be life-threatening or may cause temporary or permanent disability or death. The risks associated with taking oral contraceptives increase significantly if you:

- Smoke
- Have high blood pressure, diabetes, high cholesterol, or are obese
- Have or have had clotting disorders, heart attack, stroke, angina pectoris, cancer of the breast or sex organs, jaundice or malignant or benign liver tumors

You should not take the pill if you are pregnant or have unexplained vaginal bleeding.

Although cardiovascular disease risks may be increased with oral contraceptive use after age 40 in healthy, non-smoking women (even with the newer low-dose formulations), there are also greater potential health risks associated with pregnancy in older women.

BOXED WARNING

Cigarette smoking increases the risk of serious adverse effects on the heart and blood vessels from oral contraceptive use. This risk increases with age and with the amount of smoking (15 or more cigarettes per day has been associated with a significantly increased risk) and is quite marked in women over 35 years of age. Women who use oral contraceptives should not smoke.

Most side effects of the pill are not serious. The most common are nausea, vomiting, bleeding or spotting between menstrual periods, weight gain, breast tenderness, and difficulty wearing contact lenses. These side effects, especially nausea and vomiting, may decrease or subside within the first three months of use.

The serious side effects of the pill occur very infrequently, especially if you are in good health and do not smoke. However, you should know that the following medical conditions have been associated with or made worse by the pill:

1. Blood clots in the legs (thrombophlebitis), lungs (pulmonary embolism), stoppage or rupture of a blood vessel in the brain (stroke), blockage of blood vessels in the heart (heart attack or angina pectoris), or other organs of the body. As mentioned above, smoking increases the risk of heart attacks and strokes and subsequent serious medical consequences. Women with migraine also may be at increased risk of stroke when taking the pill.

2. Liver tumors, which may rupture and cause severe bleeding. A possible but not definite association has been found with the pill and liver cancer. However, liver cancers are extremely rare. The chance of developing liver cancer from using the pill is thus even rarer.

3. High blood pressure, although blood pressure usually returns to normal when the pill is stopped.

The symptoms associated with these serious side effects are discussed in the DETAILED PATIENT INFORMATION leaflet given to you with your supply of pills. Notify your healthcare provider if you notice any unusual physical disturbances while taking the pill. In addition, drugs such as rifampin, as well as some anticonvulsants and some antibiotics, and herbal preparations containing St. John's Wort (hypericum perforatum), may decrease oral contraceptive effectiveness.

Breast cancer has been diagnosed slightly more often in women who use the pill than in women of the same age who do not use the pill. This very small increase in the number of breast cancer diagnoses gradually disappears during the 10 years after stopping use of the pill. It is not known whether the difference is caused by the pill. It may be that women taking the pill are examined more often, so that breast cancer is more likely to be detected. You should have regular breast examinations by a healthcare provider and examine your own breasts monthly. Tell your healthcare provider if you have a family history of breast cancer or if you have had breast nodules or an abnormal mammogram. Women who currently have or have had breast cancer should not use hormonal contraceptives because breast cancer is usually a hormone-sensitive tumor.

Some studies have found an increase in the incidence of cancer or precancerous lesions of the cervix in women who use the pill. However, this finding may be related to factors other than the use of the pill.

Taking the combination pill provides some important noncontraceptive health benefits. These include less painful menstruation, less menstrual blood loss and anemia, fewer pelvic infections, and fewer cancers of the ovary and the lining of the uterus.

Be sure to discuss any medical condition you may have with your healthcare provider. Your healthcare provider will take a medical and family history before prescribing oral contraceptives and will examine you. The physical examination may be delayed to another time if you request it and the healthcare provider believes that it is a good medical practice to postpone it. You should be reexamined at least once a year while taking oral contraceptives. The DETAILED PATIENT INFORMATION leaflet gives you further information which you should read and discuss with your healthcare provider.

DOSAGE AND ADMINISTRATION

HOW TO TAKE FEMCON Fe

BOXED WARNING

IMPORTANT POINTS TO REMEMBER

BEFORE YOU START TAKING YOUR PILLS:

1. BE SURE TO READ THESE DIRECTIONS:
  - Before you start taking your pills
  - Anytime you are not sure what to do
2. THE PILL MAY BE SWALLOWED WHOLE OR CHEWED AND SWALLOWED. IF THE PILL IS CHEWED, YOU SHOULD DRINK A FULL GLASS (8 OUNCES) OF LIQUID IMMEDIATELY AFTER SWALLOWING.
3. TAKE ONE PILL EVERY DAY AT THE SAME TIME. If you miss pills you could get pregnant. This includes starting the pack late. The more pills you miss, the more likely you are to get pregnant.
4. MANY WOMEN HAVE SPOTTING OR LIGHT BLEEDING, OR MAY FEEL SICK TO THEIR STOMACH DURING THE FIRST 1-3 PACKS OF PILLS.
  If you have spotting or light bleeding or feel sick to your stomach, do not stop taking the pill. The problem will usually go away. If it doesn't go away, check with your healthcare provider.
5. MISSING PILLS CAN ALSO CAUSE SPOTTING OR LIGHT BLEEDING, even when you make up these missed pills.
  On the days you take 2 pills to make up for missed pills, you could also feel a little sick to your stomach.
6. IF YOU HAVE VOMITING (within 3 to 4 hours after you take your pill), you should follow the instructions for WHAT TO DO IF YOU MISS PILLS. IF YOU HAVE DIARRHEA or IF YOU TAKE CERTAIN MEDICINES, including some antibiotics, or the herbal supplement St. John’s Wort, your pills may not work as well. Use a back-up method of birth control (such as condoms or spermicide) until you check with your healthcare provider.
7. IF YOU HAVE TROUBLE REMEMBERING TO TAKE THE PILL, talk to your healthcare provider about how to make pill-taking easier or about using another method of birth control.
8. IF YOU HAVE ANY QUESTIONS OR ARE UNSURE ABOUT THE INFORMATION IN THIS LEAFLET, call your healthcare provider.

BOXED WARNING

BEFORE YOU START TAKING YOUR PILLS

1. DECIDE WHAT TIME OF DAY YOU WANT TO TAKE YOUR PILL.

It is important to take it at about the same time every day.

2. LOOK AT YOUR PILL PACK:

The pill pack has 21 "active" white pills (with hormones) to take for 3 weeks, followed by 7 “reminder” brown pills (without hormones) to take for 1 week.

3. ALSO FIND:

- where on the pack to start taking pills,
- in what order to take the pills (follow the arrows), and
- the week numbers as shown in the picture above.

4. BE SURE YOU HAVE READY AT ALL TIMES:

- ANOTHER KIND OF BIRTH CONTROL (such as condoms or spermicide) to use as a back-up in case you miss pills.
- AN EXTRA, FULL PILL PACK.

BOXED WARNING

WHEN TO START THE FIRST PACK OF PILLS

You have 2 choices of which day to start taking your first pack of pills. (See DAY 1 START or SUNDAY START directions below.) Decide with your healthcare provider which is the best day for you. Once you have decided which day you will begin taking your pills, immediately do the following: remove the Brief Summary from inside the pouch and look for the attached day label sheet; peel the label from the sheet which has the start day printed on the left hand side; place the label on the blister card over the pre-printed days of the week. Take your pill daily in the order indicated by the arrows on the blister card illustration shown above. Pick a time of day which will be easy to remember and take your pill at the same time each day.

DAY 1 START:

1. Take the first "active" white pill of the first pack during the first 24 hours of your period.

2. You will not need to use a back-up method of birth control, since you are starting the pill at the beginning of your period.

SUNDAY START:

1. Take the first "active" white pill of the first pack on the Sunday after your period starts, even if you are still bleeding. If your period begins on Sunday, start the pack that same day.

2. Use another method of birth control as a back-up method if you have sex anytime from the Sunday you start your first pack until the next Sunday (7 days). Condoms or spermicide are good back-up methods of birth control.

BOXED WARNING

WHAT TO DO DURING THE MONTH

1. TAKE ONE PILL AT THE SAME TIME EVERY DAY UNTIL THE PACK IS EMPTY.
  Do not skip pills even if you are spotting or bleeding between monthly periods or feel sick to your stomach (nausea).
  Do not skip pills even if you do not have sex very often.
2. WHEN YOU FINISH A PACK OF YOUR FEMCON Fe:
  Start the next pack on the day after your last brown “reminder" pill. Do not wait any days between packs.
3. WHEN YOU SWITCH FROM A DIFFERENT BRAND OF PILLS:
  If your previous brand had 21 pills, wait 7 days before starting FEMCON Fe.
  If your previous brand had 28 pills, start taking FEMCON Fe on the day after the last pill.

BOXED WARNING

WHAT TO DO IF YOU MISS PILLS

The pill may not be as effective if you miss white “active” pills, and particularly if you miss the first few or the last few white “active” pills in a pack.

If you MISS 1 white "active" pill:

1. Take it as soon as you remember. Take the next pill at your regular time. This means you may

take 2 pills in 1 day.

2. You do not need to use a back-up birth control method if you have sex.

If you MISS 2 white "active" pills in a row in WEEK 1 OR WEEK 2 of your pack:

1. Take 2 pills on the day you remember and 2 pills the next day.

2. Then take 1 pill a day until you finish the pack.

3. You COULD BECOME PREGNANT if you have sex during the 7 days after you restart your pills. You MUST use a non-hormonal birth control method (such as condoms or spermicide) as a back-up for those 7 days.

If you MISS 2 white "active" pills in a row in THE 3rd WEEK:

1. If you are a Day 1 Starter:

THROW OUT the rest of the pill pack and start a new pack that same day.

If you are a Sunday Starter:

Keep taking 1 pill every day until Sunday.

On Sunday, THROW OUT the rest of the pack and start a new pack of pills that same day.

2. You may not have your period this month but this is expected. However, if you miss your period 2 months in a row, call your healthcare provider because you might be pregnant.

3. You COULD BECOME PREGNANT if you have sex during the 7 days after you restart your pills. You MUST use a non-hormonal birth control method (such as condoms or spermicide) as a back-up for those 7 days.

If you MISS 3 OR MORE white "active" pills in a row (during the first 3 weeks):

1. If you are a Day 1 Starter:

THROW OUT the rest of the pill pack and start a new pack that same day.

If you are a Sunday Starter:

Keep taking 1 pill every day until Sunday.

On Sunday, THROW OUT the rest of the pack and start a new pack of pills that same day.

2. You may not have your period this month but this is expected. However, if you miss your period 2 months in a row, call your healthcare provider because you might be pregnant.

3. You COULD BECOME PREGNANT if you have sex on the days when you missed pills or during the first 7 days after restarting your pills. You MUST use a non-hormonal birth control method (such as condoms or spermicide) as a back-up for the first 7 days after you restart your pills.

If you forget any of the 7 brown "reminder" pills in Week 4:

1. THROW AWAY the pills you missed.

2. Keep taking 1 pill each day until the pack is empty.

3. You do not need a back-up method of birth control.

FINALLY, IF YOU ARE STILL NOT SURE WHAT TO DO ABOUT THE PILLS YOU HAVE MISSED:

1. Use a BACK-UP METHOD anytime you have sex.
2. KEEP TAKING ONE "ACTIVE" (WHITE) PILL EACH DAY until you can reach your healthcare provider.

DETAILED PATIENT PACKAGE INSERT

This product (like all oral contraceptives) is intended to prevent pregnancy. It does not protect against HIV infection (AIDS) and other sexually transmitted diseases.

INTRODUCTION

Any woman who considers using oral contraceptives (the “birth control pill” or “the pill”) should understand the benefits and risks of using this form of birth control.

Although oral contraceptives have important advantages over other methods of contraception, they have certain risks that no other method has, and some of these risks may continue after you have stopped using the oral contraceptive. This leaflet will give you much of the information you will need to make this decision and will also help you determine if you are at risk of developing any of the serious side effects of the pill. It will tell you how to use FEMCON Fe properly so that it will be as effective as possible. However, this booklet is not a replacement for a careful discussion between you and your healthcare provider. You should discuss the information provided in this booklet with your healthcare provider, both when you first start taking the pill and during your revisits. You should also follow your healthcare provider’s advice with regard to regular check-ups while you are on FEMCON Fe.

EFFECTIVENESS OF ORAL CONTRACEPTIVES

Oral contraceptives or “birth control pill” or “the pill” are used to prevent pregnancy and are more effective than most other nonsurgical methods of birth control. The chance of becoming pregnant is approximately 1% per year (1 pregnancy per 100 women per year of use) when the pills are used correctly, and no pills are missed. Typical failure rates are 5% per year (5 pregnancies per 100 women per year of use) when women who miss pills are included. The chance of becoming pregnant increases with each missed pill during a menstrual cycle.

In comparison, typical failure rates for other methods of birth control during the first year of use are as follows:

No methods: 85%

Vaginal sponge: 20 to 40%

Cervical cap: 20 to 40%

Spermicides alone: 26%

Periodic abstinence: 25%

Condom (female): 21%

Diaphragm with spermicides: 20%

Withdrawal: 19%

Condom (male): 14%

Female sterilization: 0.5%

IUD: 0.1 to 2.0%

Injectable progestogen: 0.3%

Male sterilization: 0.15%

Norplant® system: 0.05%

WHO SHOULD NOT TAKE ORAL CONTRACEPTIVES

BOXED WARNING

Cigarette smoking increases the risk of serious adverse effects on the heart and blood vessels from oral contraceptive use. This risk increases with age and with the amount of smoking (15 or more cigarettes per day has been associated with a significantly increased risk) and is quite marked in women over 35 years of age. Women who use oral contraceptives should not smoke.

Some women should not use the pill. You should not use the pill if you have or have ever had any of the following conditions:

- A history of heart attack or stroke
- A history of blood clots in the legs (thrombophlebitis), lungs (pulmonary embolism), or eyes
- A history of blood clots in the deep veins of your legs
- Chest pain (angina pectoris)
- Known or suspected breast cancer or cancer of the lining of the uterus, cervix, vagina, or certain hormonally-sensitive cancers
- Unexplained vaginal bleeding (until a diagnosis is reached by your healthcare provider)
- Yellowing of the whites of the eyes or of the skin (jaundice) during pregnancy or during previous use of the pill
- Liver tumor (benign or cancerous)
- Known or suspected pregnancy
- Heart valve or heart rhythm disorders that may be associated with formation of blood clots
- Diabetes affecting your circulation
- Uncontrolled high blood pressure
- Active liver disease with abnormal liver function tests
- Headache with neurological symptoms
- Allergy or hypersensitivity to any of the components of FEMCON Fe
- A need for surgery with prolonged bedrest

Tell your healthcare provider if you have any of the above conditions. Your healthcare provider can recommend a safer method of birth control.

OTHER CONSIDERATIONS BEFORE TAKING ORAL CONTRACEPTIVES

Tell your healthcare provider if you or any family member has ever had:

- Breast nodules, fibrocystic disease of the breast or an abnormal breast x-ray or mammogram
- Diabetes
- Elevated cholesterol or triglycerides
- High blood pressure
- Migraine or other headaches or epilepsy
- Depression
- Gallbladder, liver, heart, or kidney disease
- History of scanty or irregular menstrual periods

Women with any of these conditions should be checked often by their healthcare provider if they choose to use oral contraceptives.

Also, be sure to inform your healthcare provider if you smoke or are on any medications.

RISKS OF TAKING ORAL CONTRACEPTIVES

1. Risk of developing blood clots

Blood clots and blockage of blood vessels are the most serious side effects of taking oral contraceptives and can cause death or serious disability. In particular, a clot in the legs can cause thrombophlebitis, and a clot that travels to the lungs can cause a sudden blocking of the vessel carrying blood to the lungs. Either of these can cause death or disability. Rarely, clots occur in the blood vessels of the eye and may cause blindness, double vision, or impaired vision.

If you take oral contraceptives and need elective surgery, need to stay in bed for a prolonged illness or injury, or have recently delivered a baby, you may be at risk of developing blood clots. You should consult your healthcare provider about stopping oral contraceptives three to four weeks before surgery and not taking oral contraceptives for two weeks after surgery or during bed rest. You should also not take oral contraceptives soon after delivery of a baby. It is advisable to wait for at least four weeks after delivery if you are not breastfeeding. If you are breastfeeding, you should wait until you have weaned your child before using the pill (see the section on breastfeeding in GENERAL PRECAUTIONS).

The risk of circulatory disease in oral contraceptive users may be higher in users of high-dose pills (containing 50 micrograms or higher of ethinyl estradiol) and may be greater with longer duration of oral contraceptive use. In addition, some of these increased risks may continue for a number of years after stopping oral contraceptives. The risk of abnormal blood clotting increases with age in both users and nonusers of oral contraceptives, but the increased risk from the oral contraceptive appears to be present at all ages. For women aged 20 to 44 it is estimated that about 1 in 2,000 using oral contraceptives will be hospitalized each year because of abnormal clotting. Among nonusers in the same age group, about 1 in 20,000 would be hospitalized each year. For oral contraceptive users in general, it has been estimated that in women between the ages of 15 and 34 the risk of death due to a circulatory disorder is about 1 in 12,000 per year, whereas for nonusers the rate is about 1 in 50,000 per year. In the age group 35 to 44, the risk is estimated to be about 1 in 2,500 per year for oral contraceptive users and about 1 in 10,000 per year for nonusers.

2. Heart attacks and strokes

Oral contraceptives may increase the tendency to develop strokes (stoppage or rupture of blood vessels in the brain) and angina pectoris and heart attacks (blockage of blood vessels in the heart). Any of these conditions can cause death or disability.

Smoking greatly increases the possibility of suffering heart attacks and strokes. Furthermore, smoking and the use of oral contraceptives greatly increase the chances of developing and dying of heart disease.

Women with migraine (especially migraine with aura) who take oral contraceptives also may be at higher risk of stroke.

3. Gallbladder disease

Oral contraceptive users probably have a greater risk than nonusers of having gallbladder disease, although this risk may be related to pills containing high doses of estrogens.

4. Liver tumors

In rare cases, oral contraceptives can cause benign but dangerous liver tumors. These benign liver tumors can rupture and cause fatal internal bleeding. In addition, a possible, but not definite, association has been found with the pill and liver cancers in two studies, in which a few women who developed these very rare cancers were found to have used oral contraceptives for long periods. However, liver cancers in general are extremely rare, and the chance of developing liver cancer from using the pill is thus even rarer.

5. Cancer of the breast and reproductive organs

Breast cancer has been diagnosed slightly more often in women who use the pill than in women of the same age who do not use the pill. This small increase in the number of breast cancer diagnoses gradually disappears during the 10 years after stopping use of the pill. It is not known whether the difference is caused by the pill. It may be that women taking the pill are examined more often, so that breast cancer is more likely to be detected. You should have regular breast examinations by a healthcare provider and examine your own breasts monthly. Tell your healthcare provider if you have a family history of breast cancer or if you have had breast nodules or an abnormal mammogram.

Women who currently have or have had breast cancer should not use oral contraceptives because breast cancer is usually a hormone-sensitive tumor.

Some studies have found an increase in the incidence of cancer or precancerous lesions of the cervix in women who use oral contraceptives. However, this finding may be related to factors other than the use of oral contraceptives. There is insufficient evidence to rule out the possibility that the pill may cause such cancers.

6. Lipid metabolism and inflammation of the pancreas

In patients with inherited defects of lipid metabolism, there have been reports of significant elevations of plasma triglycerides during estrogen therapy. This has led to pancreatitis in some cases.

ESTIMATED RISK OF DEATH FROM A BIRTH CONTROL METHOD OR PREGNANCY

All methods of birth control and pregnancy are associated with a risk of developing certain diseases which may lead to disability or death. An estimate of the number of deaths associated with different methods of birth control and pregnancy has been calculated and is shown in the following table.

ANNUAL NUMBER OF BIRTH-RELATED OR METHOD-RELATED DEATHS ASSOCIATED
WITH CONTROL OF FERTILITY PER 100,000 NONSTERILE WOMEN,
BY FERTILITY CONTROL METHOD ACCORDING TO AGE
 | AGE
Method of control; and outcome | 15-19 | 20-24 | 25-29 | 30-34 | 35-39 | 40-44
No fertility control methods* | 7.0 | 7.4 | 9.1 | 14.8 | 25.7 | 28.2
Oral contraceptives; nonsmoker** | 0.3 | 0.5 | 0.9 | 1.9 | 13.8 | 31.6
Oral contraceptives; smoker** | 2.2 | 3.4 | 6.6 | 13.5 | 51.1 | 117.2
IUD** | 0.8 | 0.8 | 1.0 | 1.0 | 1.4 | 1.4
Condom* | 1.1 | 1.6 | 0.7 | 0.2 | 0.3 | 0.4
Diaphragm/spermicide* | 1.9 | 1.2 | 1.2 | 1.3 | 2.2 | 2.8
Periodic abstinence* | 2.5 | 1.6 | 1.6 | 1.7 | 2.9 | 3.6
*Deaths are birth related
**Deaths are method related

In the above table, the risk of death from any birth control method is less than the risk of childbirth, except for oral contraceptive users over the age of 35 who smoke and pill users over the age of 40 even if they do not smoke. It can be seen in the table that for women aged 15 to 39, the risk of death was highest with pregnancy (7-26 deaths per 100,000 women, depending on age). Among pill users who do not smoke, the risk of death was always lower than that associated with pregnancy for any age group, although over the age of 40, the risk increases to 32 deaths per 100,000 women, compared to 28 associated with pregnancy at that age. However, for pill users who smoke and are over the age of 35, the estimated number of deaths exceeds those for other methods of birth control. If a woman is over the age of 40 and smokes, her estimated risk of death is four times higher (117/100,000 women) than the estimated risk associated with pregnancy (28/100,000 women) in that age group.

The suggestion that women over 40 who don't smoke should not take oral contraceptives is based on information from older high-dose pills. An Advisory Committee of the FDA discussed this issue in 1989 and recommended that the benefits of oral contraceptive use by healthy, nonsmoking women over 40 years of age may outweigh the possible risks. Older women, as all women who take oral contraceptives, should take an oral contraceptive which contains the least amount of estrogen and progestin that is compatible with the individual patient needs.

WARNING SIGNALS

If any of these adverse conditions occur while you are taking oral contraceptives, call your healthcare provider immediately:

- Sharp chest pain, coughing of blood, or sudden shortness of breath (indicating a possible clot in the lung)
- Pain in the calf (indicating a possible clot in the leg)
- Crushing chest pain or heaviness in the chest (indicating a possible heart attack)
- Sudden severe headache or vomiting, dizziness or fainting, disturbances of vision or speech, weakness, or numbness in an arm or leg (indicating a possible stroke)
- Sudden partial or complete loss of vision (indicating a possible clot in the eye)
- Breast lumps (indicating possible breast cancer or fibrocystic disease of the breast; ask your healthcare provider to show you how to examine your breasts)
- Severe pain or tenderness in the stomach area (possibly indicating a ruptured liver tumor)
- Difficulty in sleeping, weakness, lack of energy, fatigue, or change in mood (possibly indicating severe depression)
- Jaundice or a yellowing of the skin or eyeballs, accompanied frequently by fever, fatigue, loss of appetite, dark-colored urine, or light-colored bowel movements (indicating possible liver problems)

SIDE EFFECTS OF ORAL CONTRACEPTIVES

In addition to the risks and more serious side effects discussed above (see RISKS OF TAKING ORAL CONTRACEPTIVES, ESTIMATED RISK OF DEATH FROM A BIRTH CONTROL METHOD OR PREGNANCY and WARNING SIGNALS sections), the following may also occur:

1. Irregular vaginal bleeding

Irregular vaginal bleeding or spotting may occur while you are taking FEMCON Fe. Irregular bleeding may vary from slight staining between menstrual periods to breakthrough bleeding which is a flow much like a regular period. Irregular bleeding occurs most often during the first few months of oral contraceptive use, but may also occur after you have been taking the pill for some time. Such bleeding may be temporary and usually does not indicate any serious problems. It is important to continue taking your pills on schedule. If the bleeding occurs in more than one cycle or lasts for more than a few days, talk to your healthcare provider.

2. Contact lenses

If you wear contact lenses and notice a change in vision or an inability to wear your lenses, contact your healthcare provider.

3. Fluid retention

Oral contraceptives may cause edema (fluid retention) with swelling of the fingers or ankles and may raise your blood pressure. If you experience fluid retention, contact your healthcare provider.

4. Melasma

A spotty darkening of the skin is possible, particularly of the face.

5. Other side effects

Other side effects may include nausea and vomiting, change in appetite, breast tenderness, headache, nervousness, depression, dizziness, loss of scalp hair, rash, vaginal infections, and allergic reactions.

If any of these side effects bother you, call your healthcare provider.

GENERAL PRECAUTIONS

1. Missed periods and use of oral contraceptives before or during early pregnancy

There may be times when you may not menstruate regularly after you have completed taking a cycle of pills. If you have taken your pills regularly and miss one menstrual period, continue taking your pills for the next cycle but be sure to inform your healthcare provider. If you have not taken the pills daily as instructed and missed a menstrual period, or if you missed two consecutive menstrual periods, you may be pregnant. Check with your healthcare provider immediately to determine whether you are pregnant. Stop taking FEMCON Fe if you are pregnant.

There is no conclusive evidence that oral contraceptive use is associated with an increase in birth defects when taken inadvertently during early pregnancy. Previously, a few studies had reported that oral contraceptives might be associated with birth defects but these studies have not been confirmed. Nevertheless, oral contraceptives should not be used during pregnancy. You should check with your healthcare provider about risks to your unbom child of any medication taken during pregnancy.

2. While breastfeeding

If you are breastfeeding, consult with your healthcare provider before starting oral contraceptives. Some of the drug will be passed on to the child in the milk. A few adverse effects on the child have been reported, including yellowing of the skin (jaundice) and breast enlargement. In addition, oral contraceptives may decrease the amount and quality of your milk. If possible, do not use oral contraceptives while breastfeeding. You should use another method of contraception since breastfeeding provides only partial protection from becoming pregnant, and this partial protection decreases significantly as you breastfeed for longer periods of time. You should consider starting oral contraceptives only after you have weaned your child completely.

3. Laboratory tests

If you are scheduled for any laboratory tests, tell your healthcare provider you are taking birth control pills. Certain blood tests may be affected by birth control pills.

4. Drug interactions

Certain drugs may interact with birth control pills to make them less effective in preventing pregnancy or cause an increase in breakthrough bleeding. Such drugs include rifampin, drugs used for epilepsy such as barbiturates (for example, phenobarbital), carbamazepine (Tegretol® is one brand of this drug), and phenytoin (Dilantin® is one brand of this drug), primidone (Mysoline®), topiramate (Topamax®), phenylbutazone (Butazolidin® is one brand), some drugs used for HIV such as ritonavir (Norvir®), modafinil (Provigil®) and possibly certain antibiotics (such as ampicillin and other penicillins, and tetracyclines), and herbal products containing St. John’s Wort (hypericum perforatum). You may need to use a non-hormonal method of contraception during any cycle in which you take drugs that can make oral contraceptives less effective. Be sure to tell your healthcare provider if you are taking or start taking any other medications, including nonprescription products or herbal products while taking birth control pills.

You may be at higher risk of a specific type of liver dysfunction if you take troleandomycin (Tao® capsules) and oral contraceptives at the same time.

5. Sexually transmitted diseases

This product (like all oral contraceptives) is intended to prevent pregnancy. It does not protect against transmission of HIV (AIDS) and other sexually transmitted diseases such as Chlamydia, genital herpes, genital warts, gonorrhea, hepatitis B, and syphilis.

HOW TO TAKE FEMCON Fe

BOXED WARNING

IMPORTANT POINTS TO REMEMBER

BEFORE YOU START TAKING YOUR PILLS:

1. BE SURE TO READ THESE DIRECTIONS:
  - Before you start taking your pills
  - Anytime you are not sure what to do
2. THE PILL MAY BE SWALLOWED WHOLE OR CHEWED AND SWALLOWED. IF THE PILL IS CHEWED, YOU SHOULD DRINK A FULL GLASS (8 OUNCES) OF LIQUID IMMEDIATELY AFTER SWALLOWING.
3. TAKE ONE PILL EVERY DAY AT THE SAME TIME. If you miss pills you could get pregnant.
  This includes starting the pack late. The more pills you miss, the more likely you are to get pregnant.
4. MANY WOMEN HAVE SPOTTING OR LIGHT BLEEDING, OR MAY FEEL SICK TO THEIR STOMACH DURING THE FIRST 1-3 PACKS OF PILLS.
  If you have spotting or light bleeding or feel sick to your stomach, do not stop taking the pill. The problem will usually go away. If it doesn't go away, check with your healthcare provider.
5. MISSING PILLS CAN ALSO CAUSE SPOTTING OR LIGHT BLEEDING, even when you make up these missed pills.
  On the days you take 2 pills to make up for missed pills, you could also feel a little sick to your stomach.
6. IF YOU HAVE VOMITING (within 3 to 4 hours after you take your pill), you should follow the instructions for WHAT TO DO IF YOU MISS PILLS. IF YOU HAVE DIARRHEA or IF YOU TAKE CERTAIN MEDICINES, including some antibiotics, or the herbal supplement St. John’s Wort, your pills may not work as well. Use a back-up method of birth control (such as condoms or spermicide) until you check with your healthcare provider.
7. IF YOU HAVE TROUBLE REMEMBERING TO TAKE THE PILL, talk to your healthcare provider about how to make pill-taking easier or about using another method of birth control.
8. IF YOU HAVE ANY QUESTIONS OR ARE UNSURE ABOUT THE INFORMATION IN THIS LEAFLET, call your healthcare provider.

BOXED WARNING

BEFORE YOU START TAKING YOUR PILLS

1. DECIDE WHAT TIME OF DAY YOU WANT TO TAKE YOUR PILL.

It is important to take it at about the same time every day.

2. LOOK AT YOUR PILL PACK:

The pill pack has 21 "active" white pills (with hormones) to take for 3 weeks, followed by 7 “reminder” brown pills (without hormones) to take for 1 week.

3. ALSO FIND:

- where on the pack to start taking pills,
- in what order to take the pills (follow the arrows), and
- the week numbers as shown in the picture above.

4. BE SURE YOU HAVE READY AT ALL TIMES:

- ANOTHER KIND OF BIRTH CONTROL (such as condoms or spermicide) to use as a back-up in case you miss pills.
- AN EXTRA, FULL PILL PACK.

BOXED WARNING

WHEN TO START THE FIRST PACK OF PILLS

You have 2 choices of which day to start taking your first pack of pills. (See DAY 1 START or SUNDAY START directions below.) Decide with your healthcare provider which is the best day for you. Once you have decided which day you will begin taking your pills, immediately do the following: remove the Brief Summary from inside the pouch and look for the attached day label sheet; peel the label from the sheet which has the start day printed on the left hand side; place the label on the blister card over the pre-printed days of the week. Take your pill daily in the order indicated by the arrows on the blister card illustration shown above. Pick a time of day which will be easy to remember and take your pill at the same time each day.

DAY 1 START:

1. Take the first "active" white pill of the first pack during the first 24 hours of your period.

2. You will not need to use a back-up method of birth control, since you are starting the pill at the beginning of your period.

SUNDAY START:

1. Take the first "active" white pill of the first pack on the Sunday after your period starts, even if you are still bleeding. If your period begins on Sunday, start the pack that same day.

2. Use another method of birth control as a back-up method if you have sex anytime from the Sunday you start your first pack until the next Sunday (7 days). Condoms or spermicide are good back-up methods of birth control.

BOXED WARNING

WHAT TO DO DURING THE MONTH

1. TAKE ONE PILL AT THE SAME TIME EVERY DAY UNTIL THE PACK IS EMPTY.

Do not skip pills even if you are spotting or bleeding between monthly periods or feel sick to your stomach (nausea).
Do not skip pills even if you do not have sex very often.

2. WHEN YOU FINISH A PACK OF YOUR FEMCON Fe:
Start the next pack on the day after your last brown "reminder" pill. Do not wait any days between packs.

3. WHEN YOU SWITCH FROM A DIFFERENT BRAND OF PILLS:
If your previous brand had 21 pills, wait 7 days before starting FEMCON Fe.
If your previous brand had 28 pills, start taking FEMCON Fe on the day after the last pill.

BOXED WARNING

WHAT TO DO IF YOU MISS PILLS

The pill may not be as effective if you miss white “active” pills, and particularly if you miss the first few or the last few white “active” pills in a pack.

If you MISS 1 white "active" pill:

1. Take it as soon as you remember. Take the next pill at your regular time. This means you may take 2 pills in 1 day.

2. You do not need to use a back-up birth control method if you have sex.

If you MISS 2 white "active" pills in a row in WEEK 1 OR WEEK 2 of your pack:

1. Take 2 pills on the day you remember and 2 pills the next day.

2. Then take 1 pill a day until you finish the pack.

3. You COULD BECOME PREGNANT if you have sex during the 7 days after you restart your pills. You MUST use a non-hormonal birth control method (such as condoms or spermicide) as a back-up for those 7 days.

If you MISS 2 white "active" pills in a row in THE 3rd WEEK:

1. If you are a Day 1 Starter:

THROW OUT the rest of the pill pack and start a new pack that same day.

If you are a Sunday Starter:

Keep taking 1 pill every day until Sunday.

On Sunday, THROW OUT the rest of the pack and start a new pack of pills that same day.

2. You may not have your period this month but this is expected. However, if you miss your period 2 months in a row, call your healthcare provider because you might be pregnant.

3. You COULD BECOME PREGNANT if you have sex during the 7 days after you restart your pills. You MUST use a non-hormonal birth control method (such as condoms or spermicide) as a back-up for those 7 days.

If you MISS 3 OR MORE white "active" pills in a row (during the first 3 weeks):

1. If you are a Day 1 Starter:

THROW OUT the rest of the pill pack and start a new pack that same day.

If you are a Sunday Starter:

Keep taking 1 pill every day until Sunday.

On Sunday, THROW OUT the rest of the pack and start a new pack of pills that same day.

2. You may not have your period this month but this is expected. However, if you miss your period 2 months in a row, call your healthcare provider because you might be pregnant.

3. You COULD BECOME PREGNANT if you have sex on the days when you missed pills or during the first 7 days after restarting your pills. You MUST use a non-hormonal birth control method (such as condoms or spermicide) as a back-up for the first 7 days after you restart your pills.

If you forget any of the 7 brown "reminder" pills in Week 4:

1. THROW AWAY the pills you missed.

2. Keep taking 1 pill each day until the pack is empty.

3. You do not need a back-up method of birth control.

FINALLY, IF YOU ARE STILL NOT SURE WHAT TO DO ABOUT THE PILLS YOU HAVE MISSED:

1. Use a BACK-UP METHOD anytime you have sex.

2. KEEP TAKING ONE "ACTIVE" (WHITE) PILL EACH DAY until you can reach your healthcare provider.

GENERAL

1. Pregnancy due to pill failure

If taken every day as directed, the incidence of pill failure resulting in pregnancy is approximately 1% per year (one pregnancy per 100 women per year), but more typical failure rates are about 5% per year (5 pregnancies per 100 women per year). If pregnancy does occur, the risk to the fetus is minimal.

2. Pregnancy after stopping the pill

There may be some delay in becoming pregnant after you stop using oral contraceptives, especially if you had irregular menstrual cycles before you used oral contraceptives. It may be advisable to postpone conception until you begin menstruating regularly once you have stopped taking the pill and desire pregnancy.

There does not appear to be any increase in birth defects in newborn babies when pregnancy occurs soon after stopping the pill.

3. Overdosage

Serious ill effects have not been reported following ingestion of large doses of oral contraceptives by young children. Overdosage may cause nausea and withdrawal bleeding in females. In case of overdosage, contact your healthcare provider or pharmacist.

4. Other information

Your healthcare provider will take a medical and family history before prescribing oral contraceptives and will examine you. The physical examination may be delayed to another time if you request it and the healthcare provider believes that it is a good medical practice to postpone it. You should be reexamined at least once a year. Be sure to inform your healthcare provider if there is a family history of any of the conditions listed previously in this leaflet. Be sure to keep all appointments with your healthcare provider, because this is a time to determine if there are early signs of side effects of oral contraceptive use.

Do not use this drug for any condition other than the one for which it was prescribed. This drug has been prescribed specifically for you; do not give it to others who may want birth control pills.

HEALTH BENEFITS FROM ORAL CONTRACEPTIVES

In addition to preventing pregnancy, use of oral contraceptives may provide certain benefits. They are:

- Menstrual cycles may become more regular
- Blood flow during menstruation may be lighter and less iron may be lost. Therefore, anemia due to iron deficiency is less likely to occur
- Pain or other symptoms during menstruation may be encountered less frequently
- Ovarian cysts may occur less frequently
- Ectopic (tubal) pregnancy may occur less frequently
- Noncancerous cysts or lumps in the breast may occur less frequently
- Acute pelvic inflammatory disease may occur less frequently
- Oral contraceptive use may provide some protection against developing two forms of cancer: cancer of the ovaries and cancer of the lining of the uterus

If you want more information about birth control pills, ask your healthcare provider or pharmacist. They have a more technical leaflet called the Professional Labeling, which you may wish to read.

Manufactured by:
Warner Chilcott Company, LLC
Fajardo, PR 00738
Marketed by:
Warner Chilcott (US), LLC
Rockaway, NJ 07866
1-800-521-8813

To report SUSPECTED ADVERSE REACTIONS, contact Warner Chilcott at 1-800-521-8813 or FDA at 1-800-FDA-1088 or www.fda.gov/medwatch.

0482G045 Revised April 2009

US Patent 6,667,050

Relabeling of "Additional Barcode Label" by:
Physicians Total Care, Inc.
Tulsa, OK 74146

PRINCIPAL DISPLAY PANEL

FEMCON® Fe
(norethindrone and ethinyl estradiol tablets, chewable and ferrous fumarate tablets) 0.4 mg/35 mcg
chewable

Five PATIENT INSERTS are enclosed for your use when dispensing FEMCON® Fe.

Additional copies are available from Warner Chilcott (US), LLC
100 Enterprise Drive
Rockaway, NJ 07866

See bottom flap for
lot number and expiration date.

Each of the 21 WHITE tablets contains
norethindrone (0.4 mg)
and ethinyl estradiol (35 mcg).
Each BROWN tablets contains
ferrous fumarate (75 mg).

Dosage: 1 tablet daily as prescribed.
See Package Insert enclosed for complete
Prescribing Information.

5 Blister Cards of
28 Tablets Each
Ferrous Fumarate
tablets are not USP
for dissolution
and assay.

This product (like all oral contraceptives) is intended to prevent pregnancy. It does not protect against HIV infection (AIDS) and other sexually transmitted diseases.

Store at 25° C (77° F); excursions permitted to 15°- 30° C (59°- 86° F) [see USP Controlled Room Temperature].